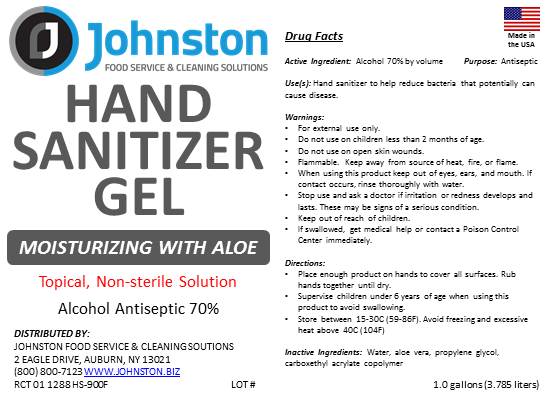 DRUG LABEL: Hand Sanitizer Gel
NDC: 75722-005 | Form: SOLUTION
Manufacturer: Rapid Cure Technologies INC
Category: otc | Type: HUMAN OTC DRUG LABEL
Date: 20200731

ACTIVE INGREDIENTS: ALCOHOL 0.7 mL/1 mL
INACTIVE INGREDIENTS: FD&C BLUE NO. 1; WATER; AMMONIUM ACRYLOYLDIMETHYLTAURATE; FD&C YELLOW NO. 5; HEPTANAL; ALOE VERA LEAF; PROPYLENE GLYCOL

Active Ingredient(s)

Alcohol 70% by volume. Purpose: Antiseptic

Purpose

Antiseptic

Use

Hand Sanitizer to help reduce bacteria that potentially can cause disease.

Warnings

For external use only. Flammable. Keep away from heat or flame

Do not use

- in children less than 2 months of age
- on open skin wounds

When using this product keep out of eyes, ears, and mouth. In case of contact with eyes, rinse eyes thoroughly with water.
Stop use and ask a doctor if irritation or rash occurs. These may be signs of a serious condition.
If swallowed, get medical help or contact a Poison Control Center right away.

Stop use and ask a doctor if irritation or rash occurs. These may be signs of a serious condition.

Directions

- Place enough product on hands to cover all surfaces. Rub hands together until dry.
- Supervise children under 6 years of age when using this product to avoid swallowing.

Other information

- Store between 15-30C (59-86F)
- Avoid freezing and excessive heat above 40C (104F)

Inactive ingredients

Water (Aqua), Aloe Vera, Propylene Glycol, Carboxethyl Acrylate Crosspolymer, Fragrance, FD&C Blue #1, FD&C Yellow #5

DESCRIPTION

Hand Sanitizer Gel

Moisturizing with Aloe

Kills Harmful Bacteris and Germs

Non-sterile Solution.

Alcohol Antiseptic 70%

Topical Solution

Keep out of reach of children.

PACKAGE LABEL

3875 ML NDC: 75722-005-01